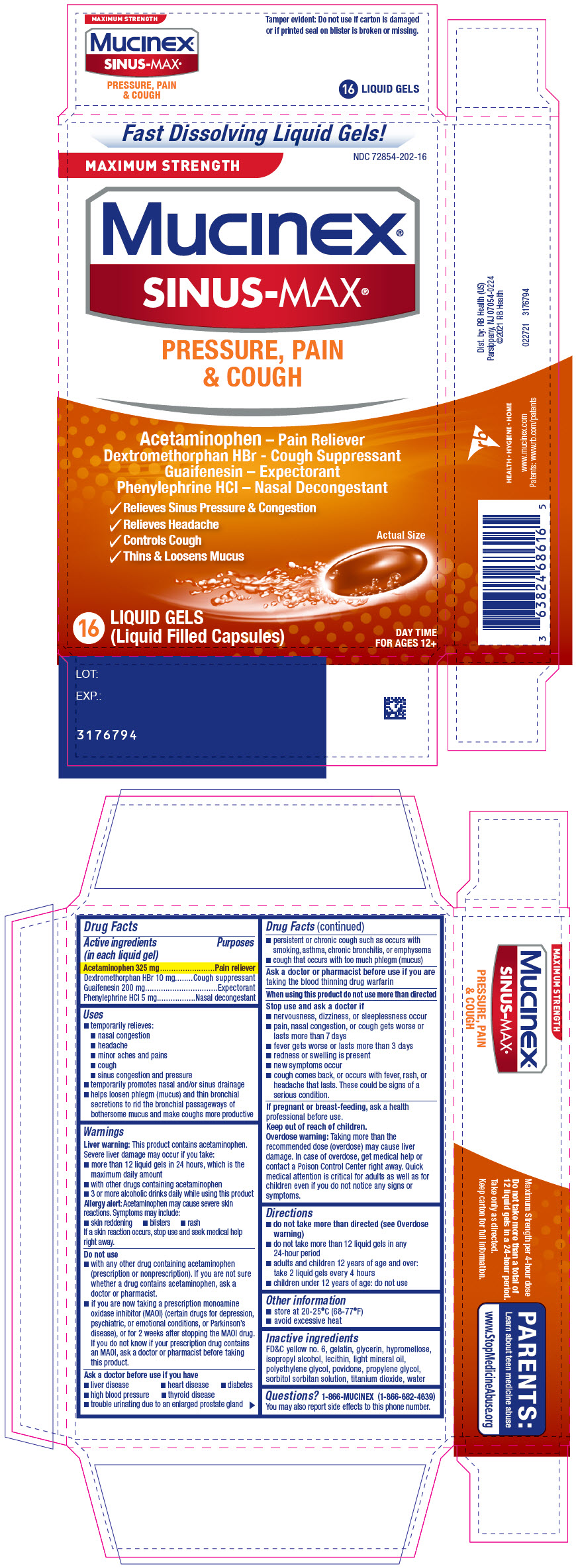 DRUG LABEL: Mucinex Sinus-Max Pressure, Pain and Cough
NDC: 72854-202 | Form: CAPSULE, LIQUID FILLED
Manufacturer: RB Health (US) LLC
Category: otc | Type: HUMAN OTC DRUG LABEL
Date: 20241223

ACTIVE INGREDIENTS: ACETAMINOPHEN 325 mg/1 1; DEXTROMETHORPHAN HYDROBROMIDE 10 mg/1 1; GUAIFENESIN 200 mg/1 1; PHENYLEPHRINE HYDROCHLORIDE 5 mg/1 1
INACTIVE INGREDIENTS: FD&C YELLOW NO. 6; GELATIN, UNSPECIFIED; GLYCERIN; HYPROMELLOSE, UNSPECIFIED; ISOPROPYL ALCOHOL; LIGHT MINERAL OIL; POLYETHYLENE GLYCOL, UNSPECIFIED; POVIDONE, UNSPECIFIED; PROPYLENE GLYCOL; TITANIUM DIOXIDE; WATER

Mucinex® Sinus-Max® Pressure, Pain & Cough
Maximum Strength

Drug Facts

ACTIVE INGREDIENT

PURPOSE

Active ingredients (in each liquid gel) | Purposes
Acetaminophen 325 mg | Pain reliever
Dextromethorphan HBr 10 mg | Cough suppressant
Guaifenesin 200 mg | Expectorant
Phenylephrine HCl 5 mg | Nasal decongestant

Uses

- temporarily relieves:
  - nasal congestion
  - headache
  - minor aches and pains
  - cough
  - sinus congestion and pressure
- temporarily promotes nasal and/or sinus drainage
- helps loosen phlegm (mucus) and thin bronchial secretions to rid the bronchial passageways of bothersome mucus and make coughs more productive

Warnings

Liver warning

This product contains acetaminophen. Severe liver damage may occur if you take:

- more than 12 liquid gels in 24 hours, which is the maximum daily amount
- with other drugs containing acetaminophen
- 3 or more alcoholic drinks daily while using this product

Allergy alert

Acetaminophen may cause severe skin reactions. Symptoms may include:

- skin reddening
- blisters
- rash

If a skin reaction occurs, stop use and seek medical help right away.

Do not use

- with any other drug containing acetaminophen (prescription or nonprescription). If you are not sure whether a drug contains acetaminophen, ask a doctor or pharmacist.
- if you are now taking a prescription monoamine oxidase inhibitor (MAOI) (certain drugs for depression, psychiatric, or emotional conditions, or Parkinson's disease), or for 2 weeks after stopping the MAOI drug. If you do not know if your prescription drug contains an MAOI, ask a doctor or pharmacist before taking this product.

Ask a doctor before use if you have

- liver disease
- heart disease
- diabetes
- high blood pressure
- thyroid disease
- trouble urinating due to an enlarged prostate gland
- persistent or chronic cough such as occurs with smoking, asthma, chronic bronchitis, or emphysema
- cough that occurs with too much phlegm (mucus)

Ask a doctor or pharmacist before use if you aretaking the blood thinning drug warfarin

When using this product do not use more than directed

Stop use and ask a doctor if

- nervousness, dizziness, or sleeplessness occur
- pain, nasal congestion, or cough gets worse or lasts more than 7 days
- fever gets worse or lasts more than 3 days
- redness or swelling is present
- new symptoms occur
- cough comes back, or occurs with fever, rash, or headache that lasts. These could be signs of a serious condition.

PREGNANCY OR BREAST FEEDING

If pregnant or breast-feeding,ask a health professional before use.

Keep out of reach of children.

Overdose warning

Taking more than the recommended dose (overdose) may cause liver damage. In case of overdose, get medical help or contact a Poison Control Center right away. Quick medical attention is critical for adults as well as for children even if you do not notice any signs or symptoms.

Directions

- do not take more than directed (see Overdose warning)
- do not take more than 12 liquid gels in any 24-hour period
- adults and children 12 years of age and over: take 2 liquid gels every 4 hours
- children under 12 years of age: do not use

Other information

- store at 20-25°C (68-77°F)
- avoid excessive heat

Inactive ingredients

FD&C yellow no. 6, gelatin, glycerin, hypromellose, isopropyl alcohol, lecithin, light mineral oil, polyethylene glycol, povidone, propylene glycol, sorbitol sorbitan solution, titanium dioxide, water

Questions?

1-866-MUCINEX (1-866-682-4639)

You may also report side effects to this phone number.

Dist. by: RB Health (US)
Parsippany, NJ 07054-0224

PRINCIPAL DISPLAY PANEL - 16 Capsule Blister Pack Carton

Fast Dissolving Liquid Gels!

NDC 72854-202-16

MAXIMUM STRENGTH

Mucinex®
SINUS-MAX®

PRESSURE, PAIN
& COUGH

Acetaminophen – Pain Reliever
Dextromethorphan HBr - Cough Suppressant
Guaifenesin – Expectorant
Phenylephrine HCl – Nasal Decongestant

- Relieves Sinus Pressure & Congestion
- Relieves Headache
- Controls Cough
- Thins & Loosens Mucus

Actual Size

16
LIQUID GELS
(Liquid Filled Capsules)

DAY TIME
FOR AGES 12+